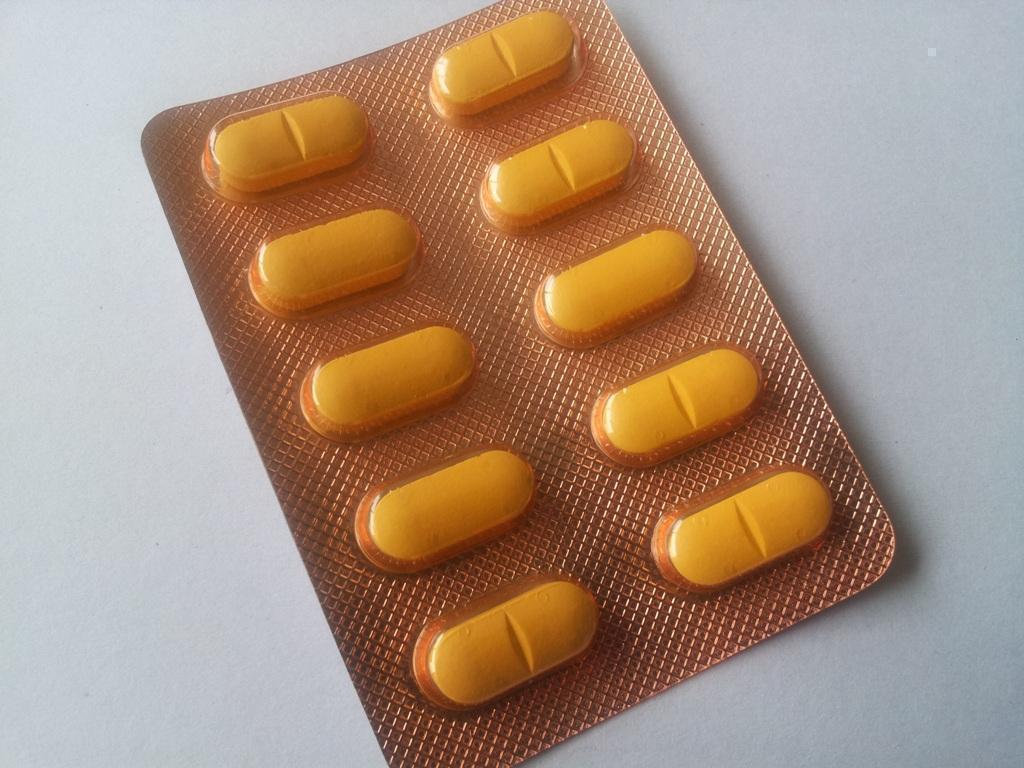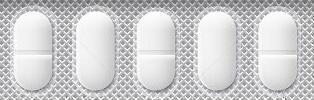 DRUG LABEL: DAYTIME NIGHTTIME COLD/FLU RELIEF
NDC: 46084-121 | Form: KIT | Route: ORAL
Manufacturer: A P J Laboratories Limited
Category: otc | Type: HUMAN OTC DRUG LABEL
Date: 20130520

ACTIVE INGREDIENTS: ACETAMINOPHEN 325 mg/1 1; DEXTROMETHORPHAN HYDROBROMIDE 10 mg/1 1; PHENYLEPHRINE HYDROCHLORIDE 5 mg/1 1; ACETAMINOPHEN 325 mg/1 1; DEXTROMETHORPHAN HYDROBROMIDE 15 mg/1 1; CHLORPHENIRAMINE MALEATE 6.25 mg/1 1
INACTIVE INGREDIENTS: CALCIUM PHOSPHATE, DIBASIC, ANHYDROUS 30 mg/1 1; STARCH, CORN 12 mg/1 1; BUTYLATED HYDROXYTOLUENE .5 mg/1 1; METHYLPARABEN .8 mg/1 1; PROPYLPARABEN .4 mg/1 1; SODIUM STARCH GLYCOLATE TYPE A POTATO 8 mg/1 1; TALC 6 mg/1 1; MAGNESIUM STEARATE 6 mg/1 1; SILICON DIOXIDE 2 mg/1 1; CROSCARMELLOSE SODIUM 3 mg/1 1; SODIUM LAURYL SULFATE 2 mg/1 1; ISOPROPYL ALCOHOL 10 mg/1 1; METHYLENE CHLORIDE 20 mg/1 1; FD&C YELLOW NO. 6 2 mg/1 1; HYPROMELLOSES 3 mg/1 1; CALCIUM PHOSPHATE, DIBASIC, ANHYDROUS 30 mg/1 1; STARCH, CORN 12 mg/1 1; BUTYLATED HYDROXYTOLUENE .5 mg/1 1; METHYLPARABEN .8 mg/1 1; PROPYLPARABEN .4 mg/1 1; SODIUM STARCH GLYCOLATE TYPE A POTATO 8 mg/1 1; TALC 6 mg/1 1; MAGNESIUM STEARATE 6 mg/1 1; SILICON DIOXIDE 2 mg/1 1; CROSCARMELLOSE SODIUM 3 mg/1 1; SODIUM LAURYL SULFATE 2 mg/1 1; ISOPROPYL ALCOHOL 10 mg/1 1; METHYLENE CHLORIDE 20 mg/1 1; FD&C YELLOW NO. 6 2 mg/1 1; HYPROMELLOSES 3 mg/1 1

ACTIVE INGREDIENT

PART 1 OF 2 DAYTIME COLD AND FLU RELIEF

Acetaminophen 325 mg

Dextromethorphan Hydrobromide 10 mg

Phenylephrine HCl 5 mg

PART 2 OF 2 NIGHTTIME COLD AND FLU RELIEF

Acetaminophen 325 mg

Dextromethorphan Hydrobromide 10 mg

Chlorpheniramine Maleate 6.25 mg

PURPOSE

Purpose for Daytime

Pain reliever/fever reducer

Cough suppressant

Nasal decongestant

Purpose for Nighttime

Pain reliever/fever reducer

Cough suppressant

Antihistamine

Keep out of reach of children

Overdose warning: Taking more than directed can cause serious health problems. In case of overdose, get medical help or contact a Poison Control Center right away. Quick medical attention is critical for adults and for children even if you do not notice any signs or symptoms.

USES

Temporarily relieves common cold/flu symptoms:
•cough due to minor throat and bronchial irritation
•sore throat
•headache
•minor aches and pains
•fever
•runny nose and sneezing (Nighttime only)
•nasal congestion (Daytime only)

WARNINGS

Liver warning: These products contain acetaminophen. Severe liver damage may occur if you take

•more than 4 doses in 24 hours, which is the maximum daily amount for these products

•with other drugs containing acetaminophen

•3 or more alcoholic drinks every day while using these products

Sore throat warning: If sore throat is severe, lasts for more than 2 days, occurs with or is followed by fever, headache, rash, nausea, or vomiting, see a doctor promptly.

Do not use

•with any other drug containing acetaminophen (prescription or nonprescription). If you are not sure whether a drug contains acetaminophen, ask a doctor or pharmacist.

•if you are now taking a prescription monoamine oxidase inhibitor (MAOI) (certain drugs for depression, psychiatric or emotional conditions, or Parkinson’s disease), or for 2 weeks after stopping the MAOI drug. If you do not know if your prescription drug contains an MAOI, ask a doctor or pharmacist before taking this product.

•to make a child sleep (Nighttime only)

DIRECTIONS

•take only as directed – see Overdose warning

•take Nighttime OR Daytime.

Nighttime tablets

•do not exceed 4 doses per 24 hours

adults and children 12 years and over swallow 2 softgels with water every 6 hrs

children 4 to under 12 years ask a doctor

children under 4 years do not use

DayTime tablets

•do not exceed 4 doses per 24 hours

adults and children 12 years and over swallow 2 softgels with water every 4 hrs

children 4 to under 12 years ask a doctor

children under 4 years do not use

•when using other Daytime or Nighttime products, carefully read each label to insure correct dosing

INACTIVE INGREDIENT

CALCIUM PHOSPHATE, DIBASIC, ANHYDROUS

STARCH, CORN

BUTYLATED HYDROXYTOLUENE

METHYLPARABEN

PROPYLPARABEN

SODIUM STARCH GLYCOLATE TYPE A POTATO

TALC

MAGNESIUM STEARATE

SILICON DIOXIDE

CROSCARMELLOSE SODIUM

SODIUM LAURYL SULFATE

ISOPROPYL ALCOHOL

METHYLENE CHLORIDE

FD and C YELLOW NO. 6

HYPROMELLOSES